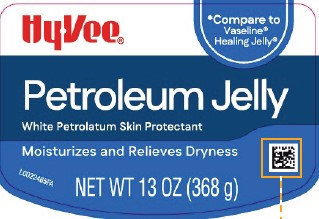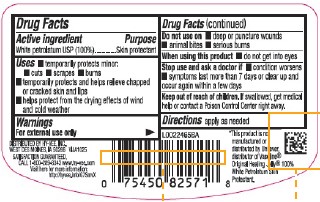 DRUG LABEL: Petroleum
NDC: 42507-069 | Form: JELLY
Manufacturer: Hy-Vee, Inc.
Category: otc | Type: HUMAN OTC DRUG LABEL
Date: 20260204

ACTIVE INGREDIENTS: PETROLATUM 1 g/1 g

Hy-Vee 069.001/069AA
Petroleum Jelly

Active ingredient

White petrolatum USP (100%)

Purpose

Skin Protectant

Uses

- temporarily protects minor: cuts - scrapes - burns
- temporarily protects and helps relieve chapped or cracked skin and lips
- helps protect from the drying effects of wind and cold weather

Warnings

For external use only

Do not use on

- deep or puncture wounds
- animal bites
- serious burns

When using this product

- do not get into eyes

Stop use and ask a doctor if

- condition worsens
- symptoms last more than 7 days or clear up and occur again within a few days

Keep out of reach of children.

If swallowed, get medical help or contact a Poison Control Center right away.

Directions

apply as needed

Disclaimer

*This product is not manufactured or distributed by Unilever, distributor of Vaseline® Original Healing Jelly® 100% White Petroleum Skin Protectant.

Adverse Reaction

DISTRIBUTED BY HY-VEE, INC.,

WEST DES MOINES, IA 50266

SATISFACTION GUARANTEED, CALL 1-800-289-8343 www.hy-vee.com

Visit here for more information http://hyvee.info

Inactive Ingredients

None

Principal display panel

Hy-Vee®

*Compare to Vaseline Healing Jelly®

Petroleum Jelly

White Petrolatum Skin Protectant

Moisturizes and Relieves Dryness

NET WT 13 oz (368 g)